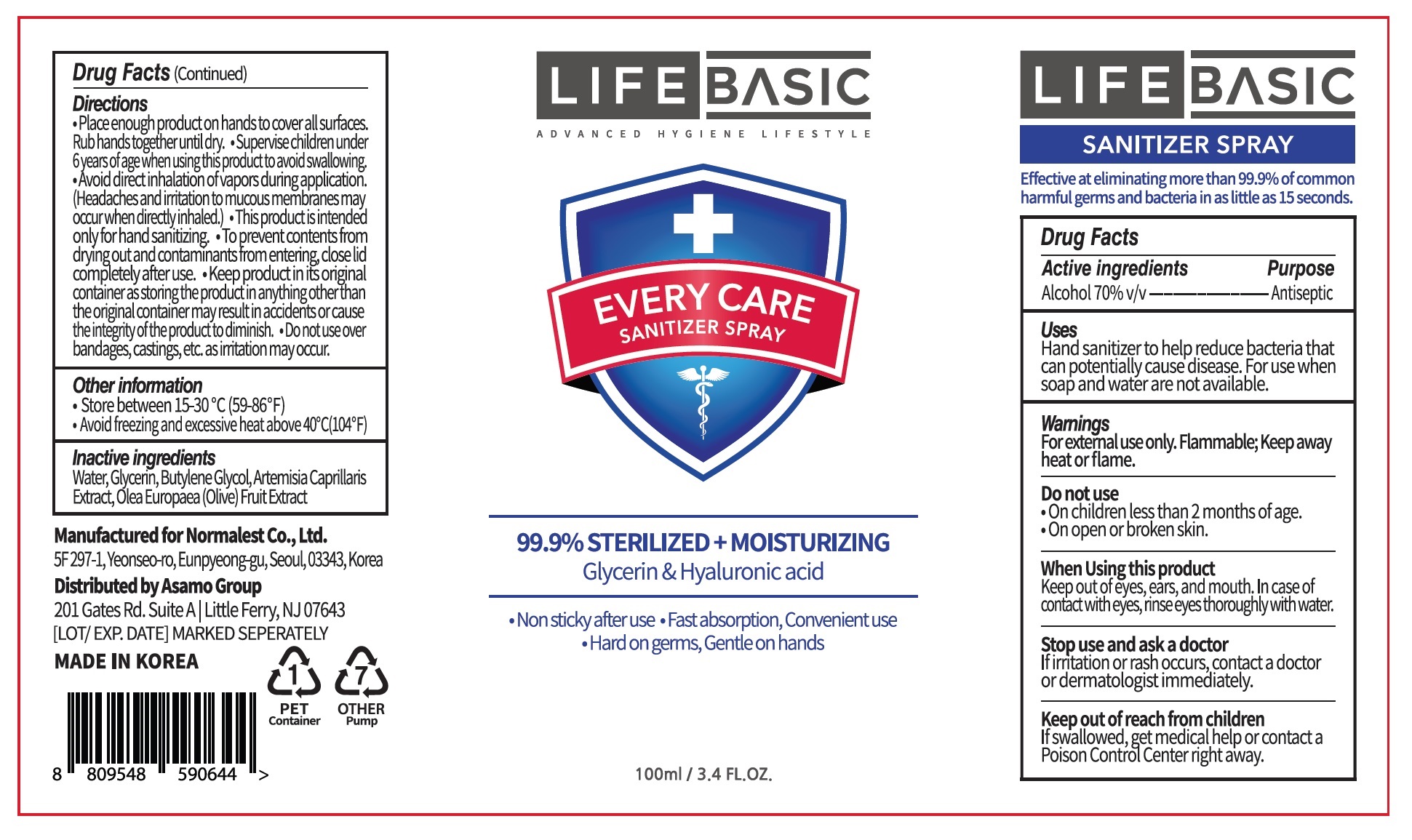 DRUG LABEL: LIFE BASIC EVERY CARE SANITIZERspray
NDC: 72284-3470 | Form: SPRAY
Manufacturer: Normalest Co., Ltd.
Category: otc | Type: HUMAN OTC DRUG LABEL
Date: 20200527

ACTIVE INGREDIENTS: ALCOHOL 70 mL/100 mL
INACTIVE INGREDIENTS: GLYCERIN; WATER; BUTYLENE GLYCOL; BLACK OLIVE; ARTEMISIA CAPILLARIS FLOWER

LIFE BASIC EVERY CARE SANITIZER SPRAY 100 ml : 72284-3470-1